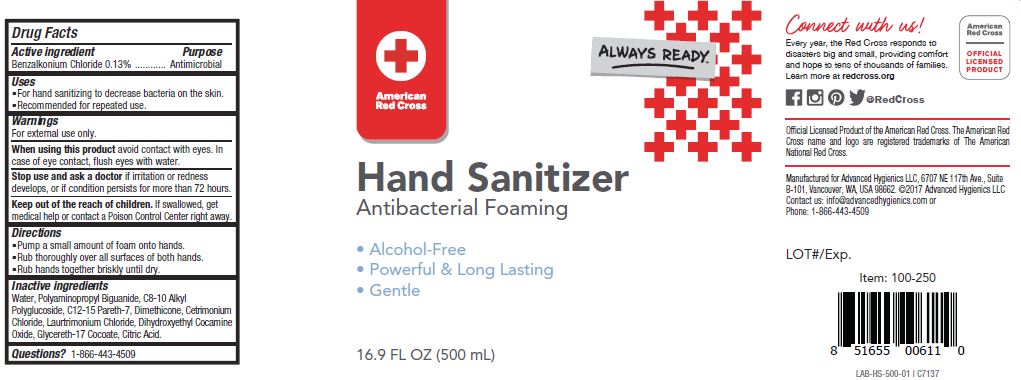 DRUG LABEL: Hand Sanitizer
NDC: 63002-004 | Form: SOLUTION
Manufacturer: Advanced Hygienics LLC
Category: otc | Type: HUMAN OTC DRUG LABEL
Date: 20170522

ACTIVE INGREDIENTS: BENZALKONIUM CHLORIDE 1.3 g/1 mL
INACTIVE INGREDIENTS: WATER; POLIHEXANIDE; CAPRYLYL GLUCOSIDE; C12-15 PARETH-7; DIMETHICONE; CETRIMONIUM CHLORIDE; LAURTRIMONIUM CHLORIDE; DIHYDROXYETHYL COCAMINE OXIDE; GLYCERETH-17 COCOATE; CITRIC ACID MONOHYDRATE

Drug Facts

Active ingredient

Benzalkonium Chloride 0.13%

Purpose

Antimicrobial

Uses

For hand sanitizing to decrease bacteria on the skin.

Recommended for repeated use.

Warnings

For external use only.

When using this product avoid contact with eyes.

In case of eye contact, flush eyes with water.

Stop use and ask a doctor if irritation or redness develops, or if condition persists for more than 72 hours.

Keep out of the reach of children.

If swallowed, get medical help or contact a Poison Control Center right away.

Directions

Pump a small amount of foam onto hands.

Rub thoroughly over all surfaces of both hands.

Rub hands together briskly until dry.

Inactive ingredients

Water, Polyaminopropyl Biguanide, C8-10 Alkyl Polyglucoside, C12-15 Pareth-7, Dimethicone, Cetrimomium Chloride, Laurtrimonium Chloride, Dihydroxyethyl Cocamine Oxide, Glycereth-17 Cocoate, Citric Acid

Questions?

1-866-443-4509

PACKAGE LABEL

American

Red Cross

Always Ready

Hand Sanitizer

Antibacterial Foaming

Alcohol-Free

Powerful and Long Lasting

Gentle

16.9 FL OZ (500 mL)